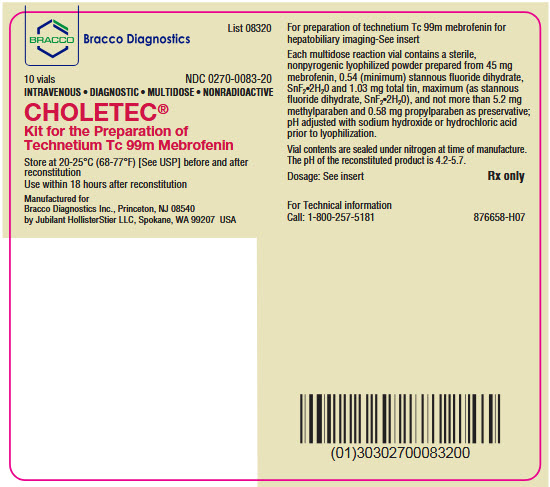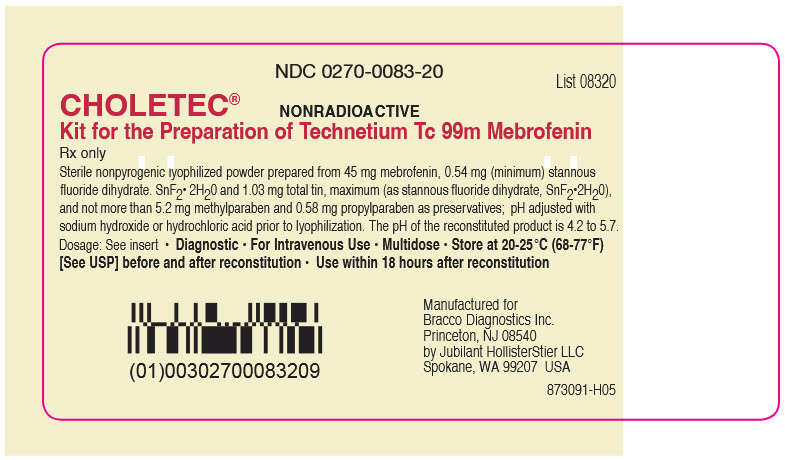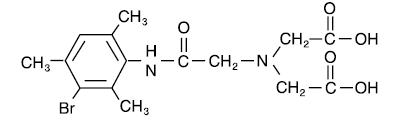 DRUG LABEL: Choletec
NDC: 0270-0083 | Form: INJECTION, POWDER, LYOPHILIZED, FOR SOLUTION
Manufacturer: Bracco Diagnostics Inc
Category: prescription | Type: HUMAN PRESCRIPTION DRUG LABEL
Date: 20251129

ACTIVE INGREDIENTS: MEBROFENIN 45 mg/1 1
INACTIVE INGREDIENTS: STANNOUS FLUORIDE 0.54 mg/1 1; METHYLPARABEN 5.2 mg/1 1; PROPYLPARABEN 0.58 mg/1 1

CHOLETEC
Kit for the Preparation of Technetium Tc 99m Mebrofenin

For Diagnostic Use

DESCRIPTION

Each reaction vial contains a nonradioactive, sterile, nonpyrogenic mixture of 45 mg mebrofenin, 0.54 mg (minimum) stannous fluoride dihydrate, SnF2•2H2O and 1.03 mg total tin, maximum (as stannous fluoride dihydrate, SnF2•2H2O), not more than 5.2 mg methylparaben, and 0.58 mg propylparaben. The pH is adjusted with sodium hydroxide or hydrochloric acid prior to lyophilization. The contents of the vial are lyophilized and sealed under nitrogen at the time of manufacture.

The pH of the reconstituted product is 4.2 to 5.7.

The structure of mebrofenin (2,2’-[[2-[(3-Bromo-2,4,6-trimethylphenyl)-amino]-2-oxoethyl]imino] bisacetic acid) is shown below:

When sterile, pyrogen-free sodium pertechnetate Tc 99m injection is added to the vial, the diagnostic agent Technetium Tc 99m Mebrofenin is formed for administration by intravenous injection.

PHYSICAL CHARACTERISTICS

Technetium Tc 99m decays by isomeric transition with a physical half-life of 6.02 hours.^1 The principal photon that is useful for detection and imaging studies is listed in Table 1.

TABLE 1
Principal Radiation Emission Data
Radiation | Mean % per Disintegration | Mean Energy (keV)
Gamma-2 | 89.07 | 140.5
^1Kocher, David C., “Radioactive Decay Data Tables”, DOE/ TIC-11026, (1981) p.108.

External Radiation

The specific gamma ray constant for Tc 99m is 0.78 R/hour-millicurie at 1 cm. The first half value layer is 0.017 cm of lead (Pb). A range of values for the relative attenuation of the radiation emitted by this radionuclide that results from interposition of various thicknesses of Pb is shown in Table 2. To facilitate control of the radiation exposure from millicurie amounts of this radionuclide, the use of a 0.25 cm thickness of Pb will attenuate the radiation emitted by a factor of about 1,000.

TABLE 2
Radiation Attenuation by Lead Shielding
Shield Thickness (Pb) cm | Coefficient of Attenuation
0.017 | 0.5
0.08 | 10^-1
0.16 | 10^-2
0.25 | 10^-3
0.33 | 10^-4

To correct for physical decay of technetium Tc 99m, the fractions that remain at selected intervals after the time of calibration are shown in Table 3.

TABLE 3
Physical Decay Chart: Tc 99m half-life 6.02 hours
Hours | Fraction Remaining | Hours | Fraction Remaining
0* | 1.000 | 7 | 0.447
1 | 0.891 | 8 | 0.398
2 | 0.794 | 9 | 0.355
3 | 0.708 | 10 | 0.316
4 | 0.631 | 11 | 0.282
5 | 0.562 | 12 | 0.251
6 | 0.501 | 18 | 0.126
*Calibration time

CLINICAL PHARMACOLOGY

Mebrofenin is an iminodiacetic acid (HIDA) derivative with no known pharmacologic action at the recommended doses.

Following intravenous administration in normal subjects, Technetium Tc 99m Mebrofenin was rapidly cleared from the circulation. The mean percent injected dose remaining in the blood at 10 minutes was 17%. The injected activity was cleared through the hepatobiliary system with visualization of the liver by 5 minutes and maximum liver uptake occurring at 11 minutes post-injection. Hepatic duct and gallbladder visualization occurred by 10 to 15 minutes and intestinal activity was visualized by 30 to 60 minutes in subjects with normal hepatobiliary function. The mean percent injected dose excreted in the urine during the first 3 hours was 1% (0.4 to 2.0%).

Elevated serum bilirubin levels increase renal excretion of Tc 99m HIDA agents. In two studies in which Tc 99m Mebrofenin was administered to patients having mean elevated serum bilirubin levels of 9.8 mg/dL (1.7 to 46.3 mg/dL), the mean percent injected dose excreted in the urine during the first 3 hours was 3% (0.2 to 11.5%). The mean percent injected dose excreted in the urine during 3-24 hours was 14.9% (0.4 to 34.8%).

In jaundiced patients, the percent injected dose remaining in the blood at 10 minutes may be twice as high or more than the level in normals. Hepatobiliary transit may be delayed and visualization times increased. As a consequence, the quality of the images obtained frequently diminishes.

INDICATIONS AND USAGE

Technetium Tc 99m Mebrofenin is indicated as a hepatobiliary imaging agent.

CONTRAINDICATIONS

Hypersensitivity to this compound.

WARNINGS

The theoretical possibility of allergic reactions should be considered in patients who receive multiple doses.

PRECAUTIONS

General

Contents of the reaction vial are intended only for use in the preparation of Technetium Tc 99m Mebrofenin and are not to be administered directly to the patient.

Delayed or non-visualization of the gallbladder may occur in the immediate post-prandial period or after prolonged fasting or parenteral feeding. Functional biliary obstruction may accompany chronic cholecystitis or pancreatitis. In addition, patients with hepatocellular disease may show non-visualization or delayed visualization of the gallbladder. Delayed intestinal transit may also be noted in such patients. Juvenile hepatitis may be associated with gallbladder non-visualization and the failure to visualize activity in the intestine. Administration of meperidine or morphine may delay intestinal transit of the imaging agent and may result in nonvisualization. Septic patients may show absent or delayed hepatobiliary clearance. Thus, a positive finding does not of itself permit a differential diagnosis of any of the above conditions and should be evaluated in the light of the total clinical picture and results of other diagnostic modalities.

The components of the kit are supplied sterile and nonpyrogenic. Aseptic procedures normally employed in making additions and withdrawals from sterile, nonpyrogenic containers should be used during the addition of the pertechnetate solution and the withdrawal of doses for patient administration.

The Technetium Tc 99m labeling reactions involved in preparing the agent depend on maintaining the stannous ion in the reduced state. Any oxidant present in the sodium pertechnetate Tc 99m supply may, thus, adversely affect the quality of the radiopharmaceutical. Hence, sodium pertechnetate Tc 99m containing oxidants should not be employed.

Radiopharmaceuticals should be used only by physicians who are qualified by training and experience in the safe use and handling of radionuclides.

As in the use of any radioactive material, care should be taken to minimize radiation exposure to the patient consistent with proper patient management and to ensure minimum radiation exposure to occupational workers.

Tc 99m Mebrofenin should be formulated no more than 18 hours prior to clinical use.

Carcinogenesis, Mutagenesis, Impairment of Fertility

No long term animal studies have been performed to evaluate carcinogenic potential or whether Technetium Tc 99m Mebrofenin may affect fertility in males or females.

Pregnancy

Animal reproduction studies have not been conducted with Technetium Tc 99m Mebrofenin. It is also not known whether Technetium Tc 99m Mebrofenin can cause fetal harm when administered to a pregnant woman or can affect reproductive capacity. Technetium Tc 99m Mebrofenin should be given to a pregnant woman only if the expected benefits to be gained clearly outweigh the potential hazards.

Nursing Mothers

Technetium Tc 99m is excreted in human milk during lactation. Therefore, formula feedings should be substituted for breast feedings.

Pediatric Use

Safety and effectiveness in children below the age of 18 have not be established.

ADVERSE REACTIONS

Urticaria and rash have been rarely reported with the use of Technetium Tc 99m Mebrofenin since market introduction. Rare cases of chills and nausea have been reported with related compounds. Infrequently, death has been reported in association with the use of this class of agents.

DOSAGE AND ADMINISTRATION

The suggested intravenous dose range of Technetium Tc 99m Mebrofenin in the average patient (70 kg) is:

Nonjaundiced patient: | 74-185 MBq (2-5 mCi)
Patient with serum bilirubin level greater than 1.5 mg/dL: | 111-370 MBq (3-10 mCi)

The patient dose should be measured by a suitable radioactivity calibration system immediately prior to administration.

The patient should be in a fasting state, 4 hours is preferable. False positives (non-visualization) may result if the gallbladder has been emptied by ingestion of food.

An interval of at least 24 hours should be allowed before repeat examination.

Parenteral drug products should be inspected visually for particulate matter and discoloration prior to administration whenever solution and container permit.

RADIATION DOSIMETRY

The estimated absorbed radiation doses ^1,2 to organs and tissues of an average subject (70 kg) from an intravenous injection of 370 MBq (10 millicuries) of Technetium Tc 99m Mebrofenin are shown in Table 4.

TABLE 4
Estimated Absorbed Radiation Doses†
 | Normal Subjects* |  | Severely Jaundiced Patients**
Tissue | mGy/ 370 MBq | rads/ 10 mCi | mGy/ 370 MBq | rads/ 10 mCi
Total Body | 2.0 | 0.2 | 1.7 | 0.17
Liver | 4.7 | 0.47 | 8.1 | 0.81
Gallbladder Wall | 13.7 | 1.37 | 12.5 | 1.25
Small Intestine | 29.9 | 2.99 | 16.0 | 1.60
Upper Large
Intestine Wall | 47.4 | 4.74 | 24.8 | 2.48
Lower Large
Intestine Wall | 36.4 | 3.64 | 19.7 | 1.97
Kidney | 2.2 | 0.22 | 1.9 | 0.19
Urinary Bladder
Wall | 2.9 | 0.29 | 24.2 | 2.42
Ovaries | 10.1 | 1.01 | 6.4 | 0.64
Testes | 0.5 | 0.05 | 1.1 | 0.11
Red Marrow | 3.4 | 0.34 | 2.5 | 0.25
†Method of Calculation:
(1) Loberg, M.D., Buddemeyer, E.V.: Application of pharmacokinetic modeling to the radiation dosimetry of hepatobiliary agents. In Third International Radiopharmaceutical Dosimetry Symposium, FDA No. 81-8166, U.S. Department of Health and Human Services, Public Health Service, FDA, Bureau of Radiological Health, Rockville, MD, (1981) pp. 318-332.
(2) Values for S: “S”, Absorbed Dose per Unit Cumulated Activity for Selected Radionuclides and Organs, MIRD Pamphlet No. 11 (1975).
* Bilirubin <1.5 mg/dL
Calculations assume that 98% of the injected activity is taken up by the liver; activity not removed in the urine in 24 hours is excreted in the intestines and no enterohepatic circulation of activity.
**
Bilirubin >10 mg/dL (mean 21.8 mg/dL)
Calculations assume that 66% of the injected activity is taken up by the liver; activity not removed in the urine in 24 hours is excreted in the intestines and no enterohepatic circulation of activity.

HOW SUPPLIED

Choletec (Kit for the Preparation of Technetium Tc 99m Mebrofenin) is supplied in kits of 10 reaction vials. Each vial contains a sterile, nonpyrogenic lyophilized mixture of 45 mg mebrofenin, 0.54 mg (minimum) stannous fluoride dihydrate, SnF2•2H2O and 1.03 mg total tin, maximum (as stannous fluoride dihydrate, SnF2•2H2O), not more than 5.2 mg methylparaben, and 0.58 mg propylparaben. The pH has been adjusted with hydrochloric acid or sodium hydroxide prior to lyophilization. The lyophilized vial contents are sealed under nitrogen at the time of manufacture. The pH of the reconstituted product is 4.2 to 5.7.

Kit Contents

10 sterile multidose reaction vials.
20 pressure-sensitive labels for Technetium Tc 99m Mebrofenin.
1 package insert.

Preparation

Preparation of Technetium Tc 99m Mebrofenin is done by the following aseptic procedure:

1. Waterproof gloves should be worn during the preparation procedure.
2. Place reaction vial in an appropriate lead shield.
3. Swab the rubber closure of the reaction vial with a germicide.
4. Inject 1 to 5 mL sterile additive free sodium pertechnetate Tc 99m injection containing up to 3700 MBq (100 mCi) Tc 99m into the reaction vial. Be sure to maintain a nitrogen atmosphere in the vial by not introducing air during reconstitution.
  NOTE: If sodium pertechnetate Tc 99m injection must be diluted for use with Choletec (Kit for the preparation of Technetium Tc 99m Mebrofenin), only preservative free Sodium Chloride Injection USP should be used.
5. Secure the lead shield cover. Swirl the vial gently to mix contents and let stand for 15 minutes.
6. Record the date and time of preparation on pressure-sensitive label.
7. Affix pressure-sensitive label to shield.
8. Examine vial contents. If the solution is not clear and free of particulate matter and discoloration on visual inspection, it should not be used.
9. Measure the radioactivity by a suitable calibration system and record on the shield label prior to patient administration.
10. Withdraw material with a sterile lead shielded syringe for use within 18 hours of preparation.

Storage

Store the kit as supplied at 20-25°C (68-77°F) [See USP] prior to and following reconstitution. Use within 18 hours of reconstitution.

The U.S. Nuclear Regulatory Commission has approved this reagent kit for distribution to persons licensed to use byproduct material identified in §35.200 of 10 CFR Part 35, to persons who hold an equivalent license issued by an Agreement State, and, outside the United States, to persons authorized by the appropriate authority.

Manufactured for
Bracco Diagnostics Inc.
Princeton, NJ 08540
by
Jubilant HollisterStier LLC
Spokane, WA 99207 USA

Revised December 2024

PACKAGE LABEL

Choletec® Kit for the Preparation of Technetium Tc 99m Mebrofenin Label
NDC: 0270˗0083˗20

Choletec® 10 Vials Label
NDC: 0270˗0083˗20